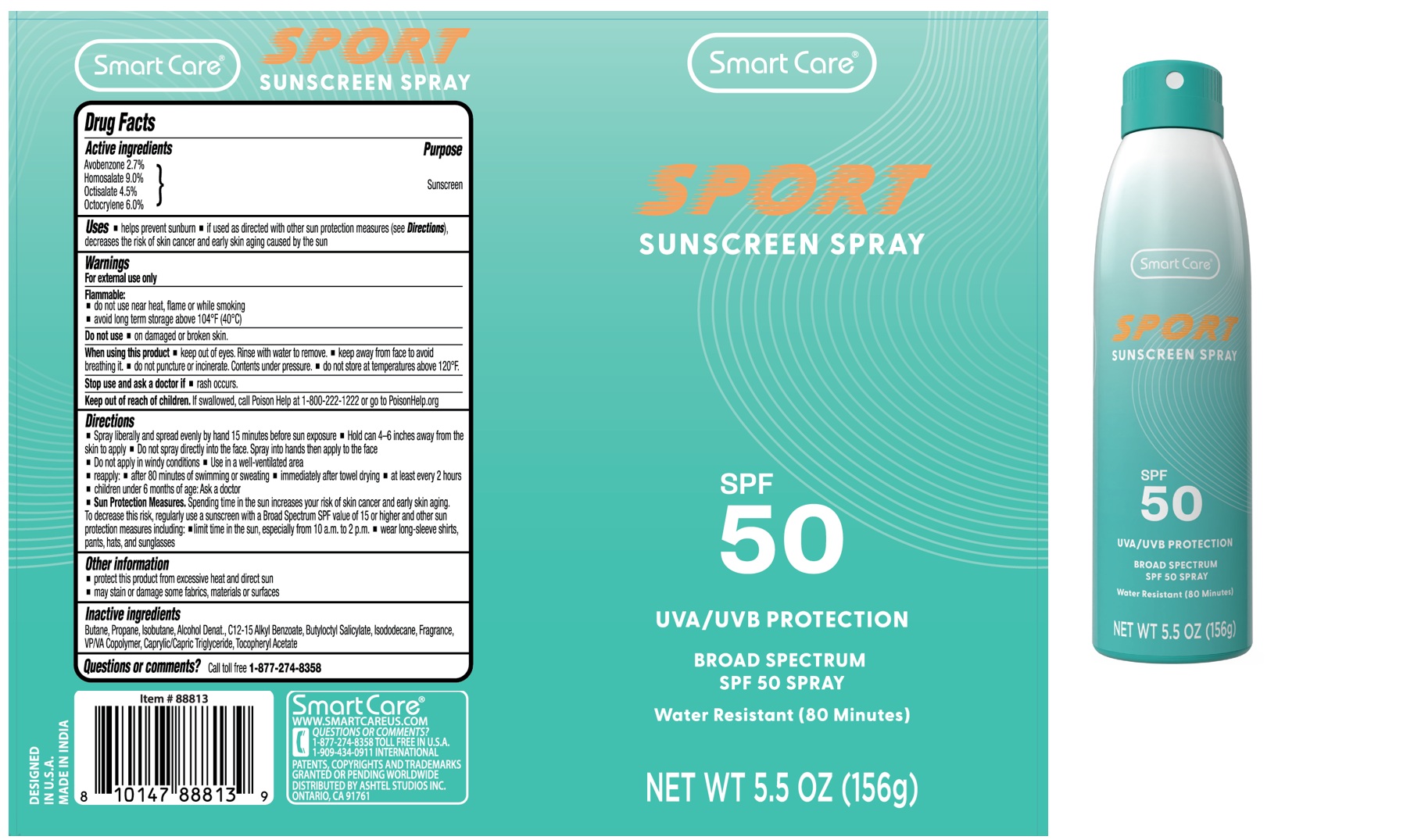 DRUG LABEL: Smart Care SPORT SUNSCREEN SPF 50
NDC: 70108-270 | Form: AEROSOL, SPRAY
Manufacturer: Ashtel Studios, Inc.
Category: otc | Type: HUMAN OTC DRUG LABEL
Date: 20260202

ACTIVE INGREDIENTS: AVOBENZONE 2.7 g/100 g; HOMOSALATE 9 g/100 g; OCTISALATE 4.5 g/100 g; OCTOCRYLENE 6 g/100 g
INACTIVE INGREDIENTS: BUTANE; PROPANE; ISOBUTANE; ALCOHOL; ALKYL (C12-15) BENZOATE; BUTYLOCTYL SALICYLATE; ISODODECANE; COPOVIDONE K25-31; MEDIUM-CHAIN TRIGLYCERIDES; .ALPHA.-TOCOPHEROL ACETATE

Smart Care® SPORT SUNSCREEN SPRAY SPF 50

Active ingredients

Avobenzone 2.7%
Homosalate 9.0%
Octisalate 4.5%
Octocrylene 6.0%

Purpose

Sunscreen

Uses

• helps prevent sunburn • if used as directed with other sun protection measures (see Directions), decreases the risk of skin cancer and early skin aging caused by the sun

Warnings

For external use only

Flammable:
• do not use near heat, flame or while smoking
• avoid long term storage above 104°F (40°C)

Do not use • on damaged or broken skin.

When using this product • keep out of eyes. Rinse with water to remove. • keep away from face to avoid breathing it. • do not puncture or incinerate. Contents under pressure. • do not store at temperatures above 120°F.

Stop use and ask a doctor if • rash occurs.

Keep out of reach of children. If swallowed, call Poison Help at 1-800-222-1222 or go to PoisonHelp.org

Directions

• Spray liberally and spread evenly by hand 15 minutes before sun exposure • Hold can 4–6 inches away from the skin to apply • Do not spray directly into the face. Spray into hands then apply to the face
• Do not apply in windy conditions • Use in a well‑ventilated area
• reapply: • after 80 minutes of swimming or sweating • immediately after towel drying • at least every 2 hours
• children under 6 months of age: Ask doctor
• Sun Protection Measures. Spending time in the sun increases your risk of skin cancer and early skin aging. To decrease this risk, regularly use a sunscreen with a Broad Spectrum SPF value of 15 or higher and other sun protection measures including: • limit time in the sun, especially from 10 a.m. to 2 p.m. • wear long‑sleeve shirts, pants, hats, and sunglasses

Other information

• protect this product from excessive heat and direct sun
• may stain or damage some fabrics, materials or surfaces

Inactive ingredients

Butane, Propane, Isobutane, Alcohol Denat., C12‑15 Alkyl Benzoate, Butyloctyl Salicylate, Isododecane, Fragrance, VP/VA Copolymer, Caprylic/Capric Triglyceride, Tocopheryl Acetate

Questions or comments?

Call toll free 1‑877‑274‑8358

UVA/UVB Protection
BROAD SPECTRUM
Water Resistant (80 Minutes)

Smart Care®
WWW.SMARTCAREUS.COM

1-909-434-0911 INTERNATIONAL

PATENTS, COPYRIGHTS AND TRADEMARKS GRANTED OR PENDING WORLDWIDE
DISTRIBUTED BY ASHTEL STUDIOS INC.
ONTARIO, CA 91761

DESIGNED IN U.S.A
MADE IN INDIA